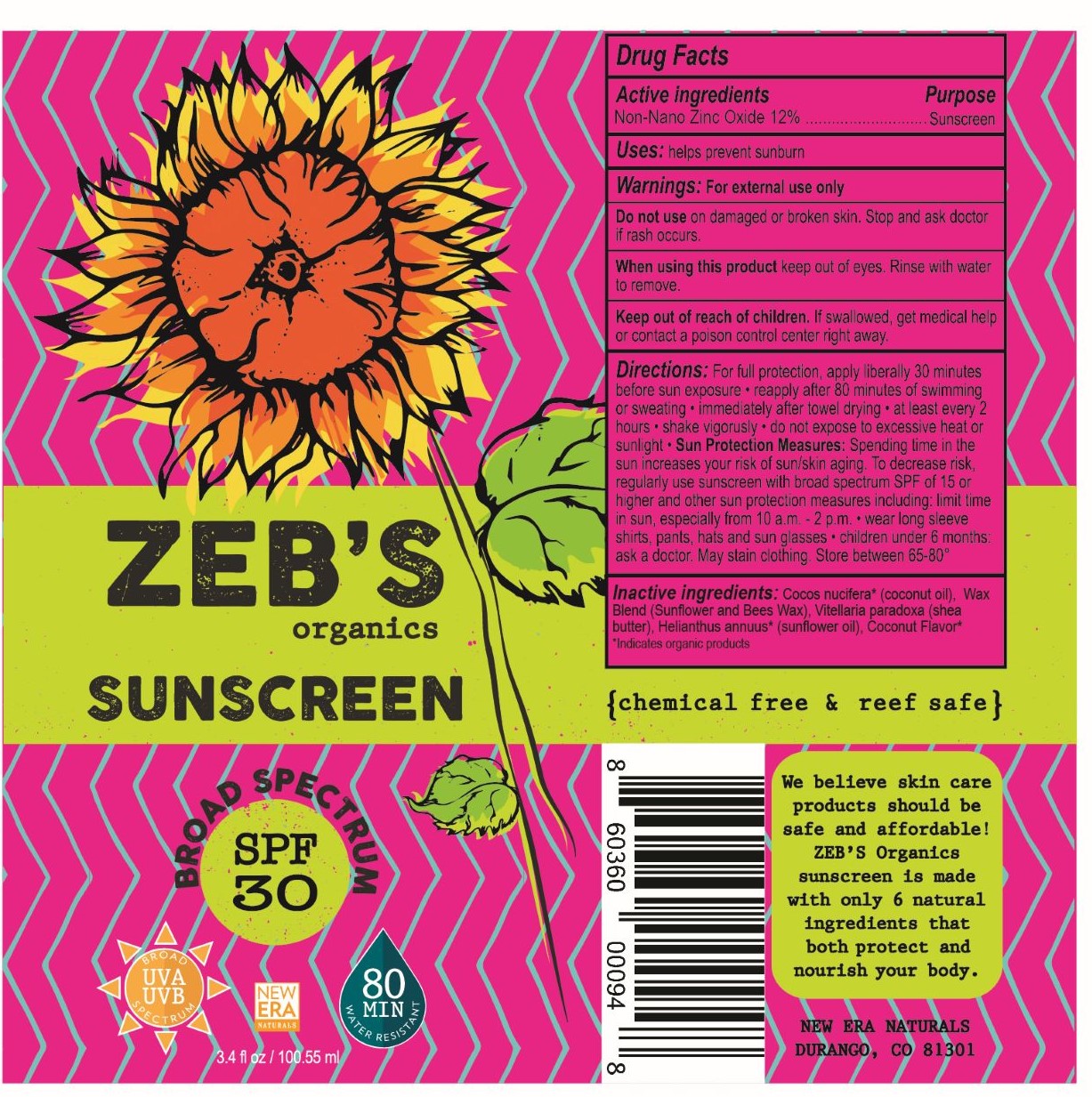 DRUG LABEL: Zebs Organics Sunscreen
NDC: 70397-2017 | Form: LOTION
Manufacturer: New Era Naturals LLC
Category: otc | Type: HUMAN OTC DRUG LABEL
Date: 20161024

ACTIVE INGREDIENTS: ZINC OXIDE 11 g/90 g
INACTIVE INGREDIENTS: COCONUT OIL 22 g/90 g; WHITE WAX 10 g/90 g; SHEA BUTTER 10 g/90 g; SUNFLOWER OIL 32 g/90 g

Zebs SPF 30 3.4oz broad spectrum sunscreen